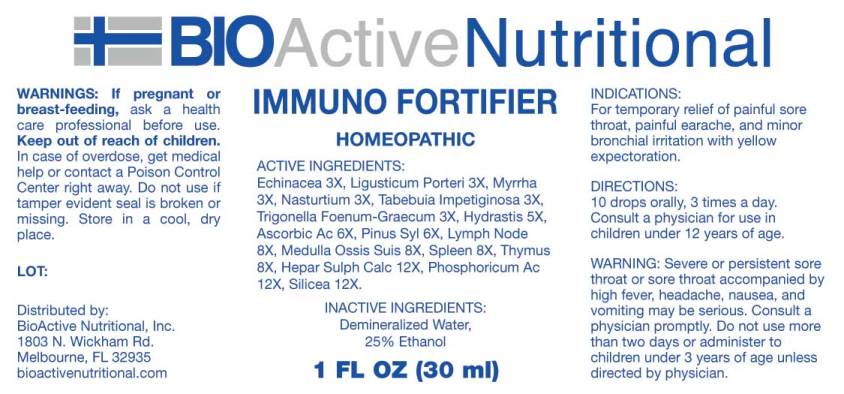 DRUG LABEL: Immuno Fortifier
NDC: 43857-0454 | Form: LIQUID
Manufacturer: BioActive Nutritional, Inc.
Category: homeopathic | Type: HUMAN OTC DRUG LABEL
Date: 20180115

ACTIVE INGREDIENTS: ECHINACEA ANGUSTIFOLIA 3 [hp_X]/1 mL; LIGUSTICUM PORTERI ROOT 3 [hp_X]/1 mL; MYRRH 3 [hp_X]/1 mL; NASTURTIUM OFFICINALE 3 [hp_X]/1 mL; TABEBUIA IMPETIGINOSA BARK 3 [hp_X]/1 mL; FENUGREEK SEED 3 [hp_X]/1 mL; GOLDENSEAL 5 [hp_X]/1 mL; ASCORBIC ACID 6 [hp_X]/1 mL; PINUS SYLVESTRIS LEAFY TWIG 6 [hp_X]/1 mL; SUS SCROFA LYMPH 8 [hp_X]/1 mL; SUS SCROFA BONE MARROW 8 [hp_X]/1 mL; SUS SCROFA SPLEEN 8 [hp_X]/1 mL; SUS SCROFA THYMUS 8 [hp_X]/1 mL; CALCIUM SULFIDE 12 [hp_X]/1 mL; PHOSPHORIC ACID 12 [hp_X]/1 mL; SILICON DIOXIDE 12 [hp_X]/1 mL
INACTIVE INGREDIENTS: WATER; ALCOHOL

Drug Facts:

ACTIVE INGREDIENTS:

Echinacea (Angustifolia) 3X, Ligusticum Porteri 3X, Myrrha 3X, Nasturtium Aquaticum 3X, Tabebuia Impetiginosa 3X, Trigonella Foenum-Graecum 3X, Hydrastis Canadensis 5X, Ascorbic Acid 6X, Pinus Sylvestris 6X, Lymph (Suis) 8X, Medulla Ossis Suis 8X, Spleen (Suis) 8X, Thymus (Suis) 8X, Hepar Sulphuris Calcareum 12X, Phosphoricum Acidum 12X, Silicea 12X.

INDICATIONS:

For temporary relief of painful sore throat, painful earache, and minor bronchial irritation with yellow expectoration.

WARNINGS:

If pregnant or breast-feeding, ask a health care professional before use.

Keep out of reach of children. In case of overdose, get medical help or contact a Poison Control Center right away.

Do not use if tamper evident seal is broken or missing.

Store in a cool, dry place.

WARNING: Severe or persistent sore throat or sore throat accompanied by high fever, headache, nausea, and vomiting may be serious.

Consult a physician promptly. Do not use more than two days or administer to children under 3 years of age unless directed by a physician.

Keep out of reach of children. In case of overdose, get medical help or contact a Poison Control Center right away.

DIRECTIONS:

10 drops orally, 3 times a day. Consult a physician for use in children under 12 years of age.

INDICATIONS:

For temporary relief of painful sore throat, painful earache, and minor bronchial irritation with yellow expectoration.

INACTIVE INGREDIENTS:

Demineralized Water, 25% Ethanol.

QUESTIONS:

Distributed by:

BioActive Nutritional, Inc.

1803 N. Wickham Rd.

Melbourne, FL 32935

PACKAGE LABEL DISPLAY:

BIOActive Nutritional

IMMUNO FORTIFIER

HOMEOPATHIC

1 FL OZ (30 ml)